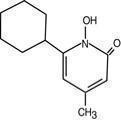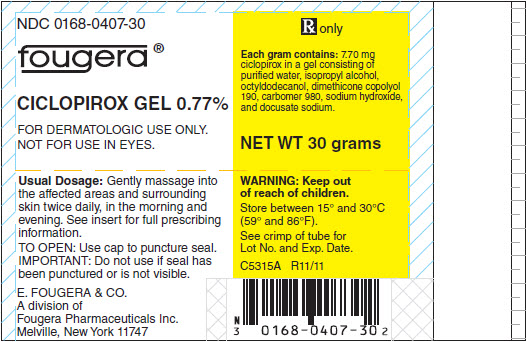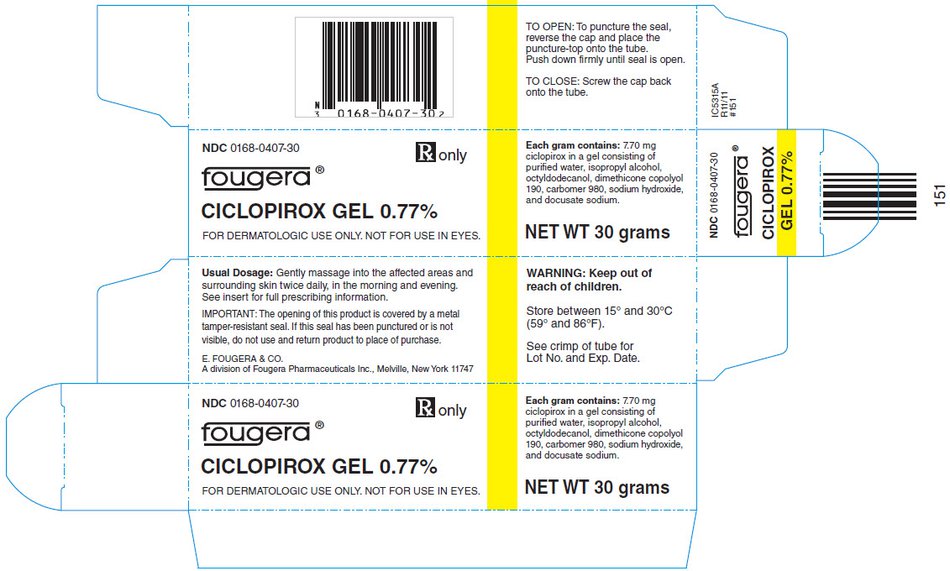 DRUG LABEL: Ciclopirox
NDC: 0168-0407 | Form: GEL
Manufacturer: E. Fougera & Co. a division of Fougera Pharmaceuticals Inc.
Category: prescription | Type: HUMAN PRESCRIPTION DRUG LABEL
Date: 20131015

ACTIVE INGREDIENTS: CICLOPIROX 7.70 mg/1 g
INACTIVE INGREDIENTS: WATER; ISOPROPYL ALCOHOL; OCTYLDODECANOL; PEG/PPG-18/18 DIMETHICONE; CARBOMER HOMOPOLYMER TYPE C (ALLYL PENTAERYTHRITOL CROSSLINKED); SODIUM HYDROXIDE; DOCUSATE SODIUM

CICLOPIROX GEL 0.77%

FOR DERMATOLOGIC USE ONLY.
Rx only
NOT FOR USE IN EYES.

DESCRIPTION:

Ciclopirox Gel 0.77% contains a synthetic antifungal agent, ciclopirox. It is intended for topical dermatologic use only.

Each gram of ciclopirox gel 0.77% contains 7.70 mg of ciclopirox in a gel consisting of purified water, isopropyl alcohol, octyldodecanol, dimethicone copolyol 190, carbomer 980, sodium hydroxide, and docusate sodium.

Ciclopirox gel 0.77% is a white, slightly fluid gel.

The chemical name for ciclopirox is 6-cyclohexyl-1-hydroxy-4-methyl-2(1H)-pyridinone, with the empirical formula C12H17NO2 and a molecular weight of 207.27. The CAS Registry Number is [29342-05-0].The chemical structure is:

CLINICAL PHARMACOLOGY:

Mechanism of Action: Ciclopirox acts by chelation of polyvalent cations (Fe^3+ or Al^3+) resulting in the inhibition of the metal-dependent enzymes that are responsible for the degradation of peroxides within the fungal cell. In vitro studies showed that ciclopirox inhibited the formation of 5-lipoxygenase inflammatory mediators (5-HETE and LTB4) and also inhibited PGE2 release in a cell culture model. In vivo, ciclopirox inhibited inflammation in an arachidonic acid-induced murine ear edema model. The clinical significance of these findings is unknown.

PHARMACOKINETICS

Pharmacokinetics: A comparative study of the pharmacokinetics of ciclopirox gel and ciclopirox cream (ciclopirox olamine) 0.77% in 18 healthy males indicated that systemic absorption of ciclopirox from ciclopirox gel was higher than that of ciclopirox cream. A 5 gm dose of ciclopirox gel produced a mean (±SD) peak serum concentration of 25.02 (±20.6) ng/mL total ciclopirox and 5 gm of ciclopirox cream produced 18.62 (±13.56) ng/mL total ciclopirox. Approximately 3% of the applied ciclopirox was excreted in the urine within 48 hours after application, with a renal elimination half-life of about 5.5 hours. In a study of ciclopirox gel, 16 men with moderate to severe tinea cruris applied approximately 15 grams/day of the gel for 14.5 days. The mean (±SD) dose-normalized values of Cmax for total ciclopirox in serum were 100 (±42) ng/mL on day 1 and 238 (±144) ng/mL on Day 15. During the 10 hours after dosing on Day 1, approximately 10% of the administered dose was excreted in the urine.

MICROBIOLOGY

Microbiology: Ciclopirox is a hydroxypyridinone antifungal agent that inhibits the growth of pathogenic dermatophytes. Ciclopirox has been shown to be active against most strains of the following microorganisms both in vitro and in clinical infections as described in the INDICATIONS AND USAGE section: Trichophyton rubrum, Trichophyton mentagrophytes, and Epidermophyton floccosum.

INDICATIONS AND USAGE:

Superficial Dermotophyte Infections - Ciclopirox gel 0.77% is indicated for the topical treatment of interdigital tinea pedis and tinea corporis due to Trichophyton rubrum, Trichophyton mentagrophytes, Epidermophyton floccosum. Seborrheic Dermatitis - Ciclopirox gel 0.77% is indicated for the topical treatment of seborrheic dermatitis of the scalp.

CONTRAINDICATIONS:

Ciclopirox gel 0.77% is contraindicated in individuals who have shown hypersensitivity to any of its components.

WARNINGS:

Ciclopirox gel 0.77% is not for ophthalmic, oral, or intravaginal use. Keep out of reach of children.

PRECAUTIONS:

If a reaction suggesting sensitivity or chemical irritation should occur with the use of ciclopirox gel 0.77%, treatment should be discontinued and appropriate therapy instituted. A transient burning sensation may occur, especially after application to sensitive areas. Avoid contact with eyes. Efficacy of ciclopirox gel 0.77% in immunosuppressed individuals has not been studied. Seborrheic dermatitis in association with acne, atopic dermatitis, Parkinsonism, psoriasis and rosacea has not been studied with ciclopirox gel 0.77%. Efficacy in the treatment of plantar and vesicular types of tinea pedis has not been established.

Information for Patients

The patient should be told the following:

1. Use ciclopirox gel 0.77% as directed by the physician. Avoid contact with the eyes and mucous membranes. Ciclopirox gel 0.77% is for external use only.
2. Use the medication for fungal infections for the full treatment time even though symptoms may have improved, and notify the physician if there is no improvement after four weeks.
3. A transient burning/stinging sensation may be felt. This may occur in approximately 15% to 20% of cases, when ciclopirox gel 0.77% is used to treat seborrheic dermatitis of the scalp.
4. Inform the physician if the area of application shows signs of increased irritation or possible sensitization (redness with itching, burning, blistering, swelling and/or oozing).
5. Avoid the use of occlusive dressings.
6. Do not use this medication for any disorder other than that for which it is prescribed.

CARCINOGENESIS AND MUTAGENESIS AND IMPAIRMENT OF FERTILITY

Carcinogenesis, Mutagenesis, Impairment of Fertility: A carcinogenicity study of ciclopirox (1% and 5% solutions in polyethylene glycol 400) in female mice dosed cutaneously twice per week for 50 weeks followed by a 6-month drug-free observation period prior to necropsy revealed no evidence of tumors at the application site. The following battery of in vitro genotoxicity tests was conducted with ciclopirox: evaluation of gene mutation in the Ames Salmonella and E. coli assays (negative); chromosome aberration assays in V79 Chinese hamster cells, with and without metabolic activation (positive); gene mutation assays in the in the HGPRT-test with V79 Chinese hamster cells (negative); and a primary DNA damage assay (i.e., unscheduled DNA synthesis assay in A549 human cells) (negative). An in vitro cell transformation assay in BALB/c 3T3 cells was negative for cell transformation. In an in vivo Chinese hamster bone marrow cytogenetic assay, ciclopirox was negative for chromosome aberrations at 5000 mg/kg.

PREGNANCY

Pregnancy - Teratogenic effects: Pregnancy Category B. Reproduction studies of ciclopirox revealed no significant evidence of impaired fertility in rats exposed orally up to 5 mg/kg body weight (approximately 5 times the maximum recommended topical human dose based on surface area). No fetotoxicity was shown due to ciclopirox in the mouse, rat, rabbit, and monkey at oral doses up to 100, 30, 30, and 50 mg/kg body weight, respectively (approximately 37.5, 30, 44, and 77 times the maximum recommended topical human dose based on surface area). By the dermal route of administration, no fetotoxicity was shown due to ciclopirox in the rat and rabbit at doses up to 120 and 100 mg/kg body weight, respectively (approximately 121 and 147 times, respectively, the maximum recommended topical human dose based on surface area). There are no adequate or well-controlled studies of topically applied ciclopirox in pregnant women. Ciclopirox gel 0.77% should be used during pregnancy only if the potential benefit justifies the potential risk to the fetus.

NURSING MOTHERS

Nursing Mothers: It is not known whether this drug is excreted in human milk. Since many drugs are excreted in human milk, caution should be exercised when ciclopirox gel 0.77% is administered to a nursing woman.

PEDIATRIC USE

Pediatric Use: The efficacy and safety of ciclopirox gel 0.77% in pediatric patients below the age of 16 years have not been established.

ADVERSE REACTIONS:

In clinical trials, 140 (39%) of 359 subjects treated with ciclopirox gel 0.77% reported adverse experiences, irrespective of relationship to test materials, which resulted in 8 subjects discontinuing treatment. The most frequent experience reported was skin burning sensation upon application, which occurred in approximately 34% of seborrheic dermatitis patients and 7% of tinea pedis patients. Adverse experiences occurring between 1% to 5% were contact dermatitis and pruritus. Other reactions that occurred in less than 1% included dry skin, acne, rash, alopecia, pain upon application, eye pain, and facial edema.

DOSAGE AND ADMINISTRATION:

Superficial Dermotophyte Infections - Gently massage ciclopirox gel 0.77% into the affected areas and surrounding skin twice daily, in the morning and evening immediately after cleaning or washing the areas to be treated. Interdigital tinea pedis and tinea corporis should be treated for four weeks. If a patient shows no clinical improvement after four weeks of treatment, the diagnosis should be reviewed. Seborrheic Dermatitis of the Scalp -Apply ciclopirox gel 0.77% to affected scalp areas twice daily, in the morning and evening for four weeks. Clinical improvement usually occurs within the first week with continuing resolution of signs and symptoms through the fourth week of treatment. If a patient shows no clinical improvement after four weeks of treatment, the diagnosis should be reviewed.

HOW SUPPLIED:

Ciclopirox Gel 0.77% is supplied in:

NDC 0168-0407-30 30 gram tube
NDC 0168-0407-46 45 gram tube
NDC 0168-0407-99 100 gram tube

Store between 15°-30°C (59°-86°F).

Fougera
PHARMACEUTICALS INC.
E. FOUGERA & CO.
A division of Fougera Pharmaceuticals Inc.
Melville, New York 11747

I2407D
R10/13
#150

PACKAGE LABEL – PRINCIPAL DISPLAY PANEL – 30 GRAM CONTAINER

NDC 0168-0407-30

Fougera®

CICLOPIROX GEL 0.77%

FOR DERMATOLOGIC USE ONLY.

NOT FOR USE IN EYES.

Rx only

NET WT 30 grams

PACKAGE LABEL – PRINCIPAL DISPLAY PANEL – 30 GRAM CARTON

NDC 0168-0407-30

Fougera®

Rx only

CICLOPIROX GEL 0.77%

FOR DERMATOLOGIC USE ONLY. NOT FOR USE IN EYES.

NET WT 30 grams